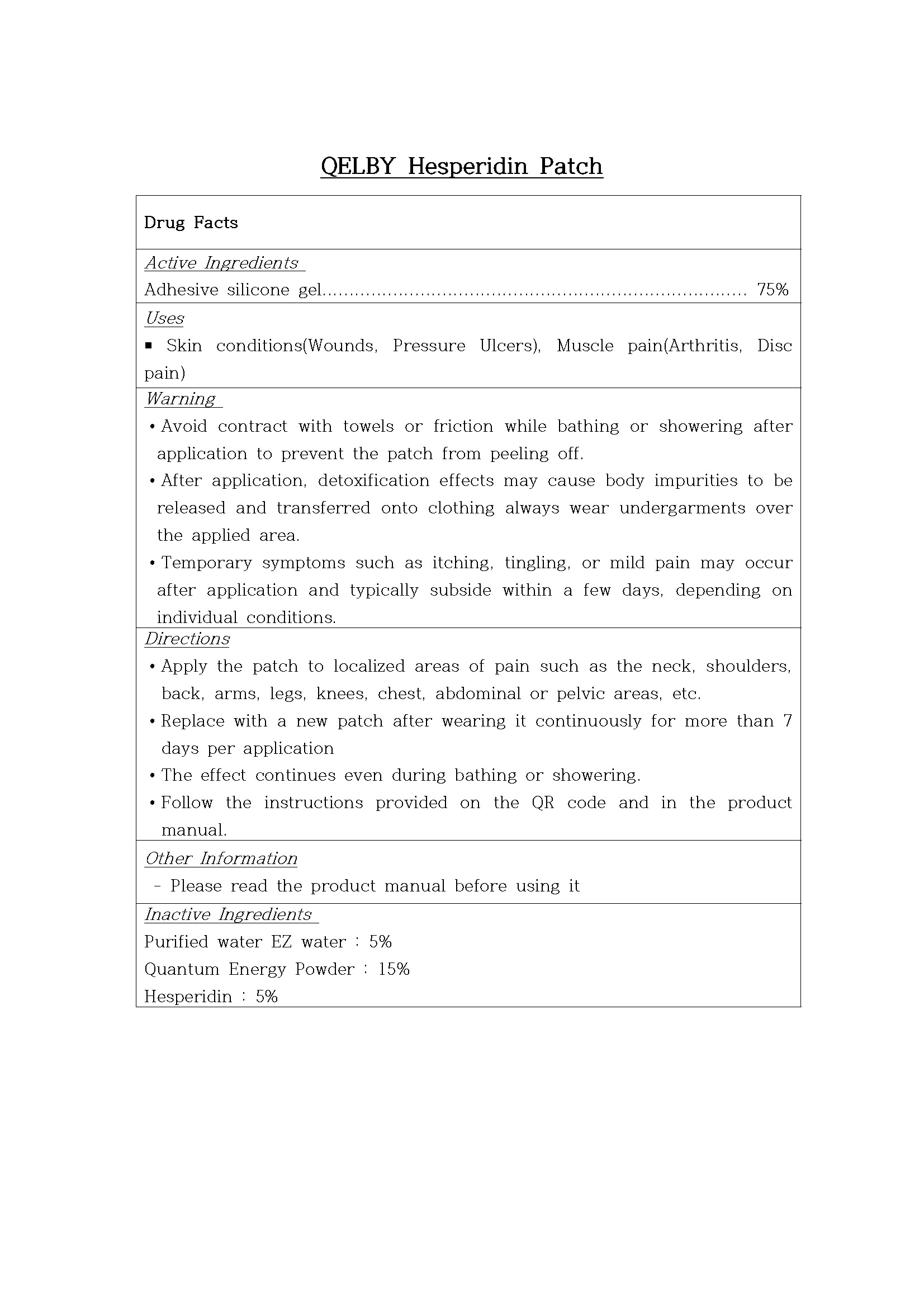 DRUG LABEL: QELBY Hesperidin Patch
NDC: 87369-0001 | Form: PATCH
Manufacturer: JD LIFE SCIENCES CO., LTD
Category: otc | Type: HUMAN OTC DRUG LABEL
Date: 20260202

ACTIVE INGREDIENTS: SILICON 75 g/100 g
INACTIVE INGREDIENTS: WATER

Drug Facts

ACTIVE INGREDIENT

Adhesive silicone gel

INACTIVE INGREDIENT

Purified water EZ water, Quantum Energy Powder, Hesperidin

PURPOSE

Skin conditions(Wounds, Pressure Ulcers), Muscle pain(Arthritis, Disc pain)

keep out of reach of the children

WARNINGS

∙Avoid contract with towels or friction while bathing or showering after application to prevent the patch from peeling off.

∙After application, detoxification effects may cause body impurities to be released and transferred onto clothing always wear undergarments over the applied area.

∙Temporary symptoms such as itching, tingling, or mild pain may occur after application and typically subside within a few days, depending on individual conditions.

INDICATIONS AND USAGE

∙Apply the patch to localized areas of pain such as the neck, shoulders, back, arms, legs, knees, chest, abdominal or pelvic areas, etc.

∙Replace with a new patch after wearing it continuously for more than 7 days per application

∙The effect continues even during bathing or showering.

∙Follow the instructions provided on the QR code and in the product manual.

DOSAGE AND ADMINISTRATION

for external use only